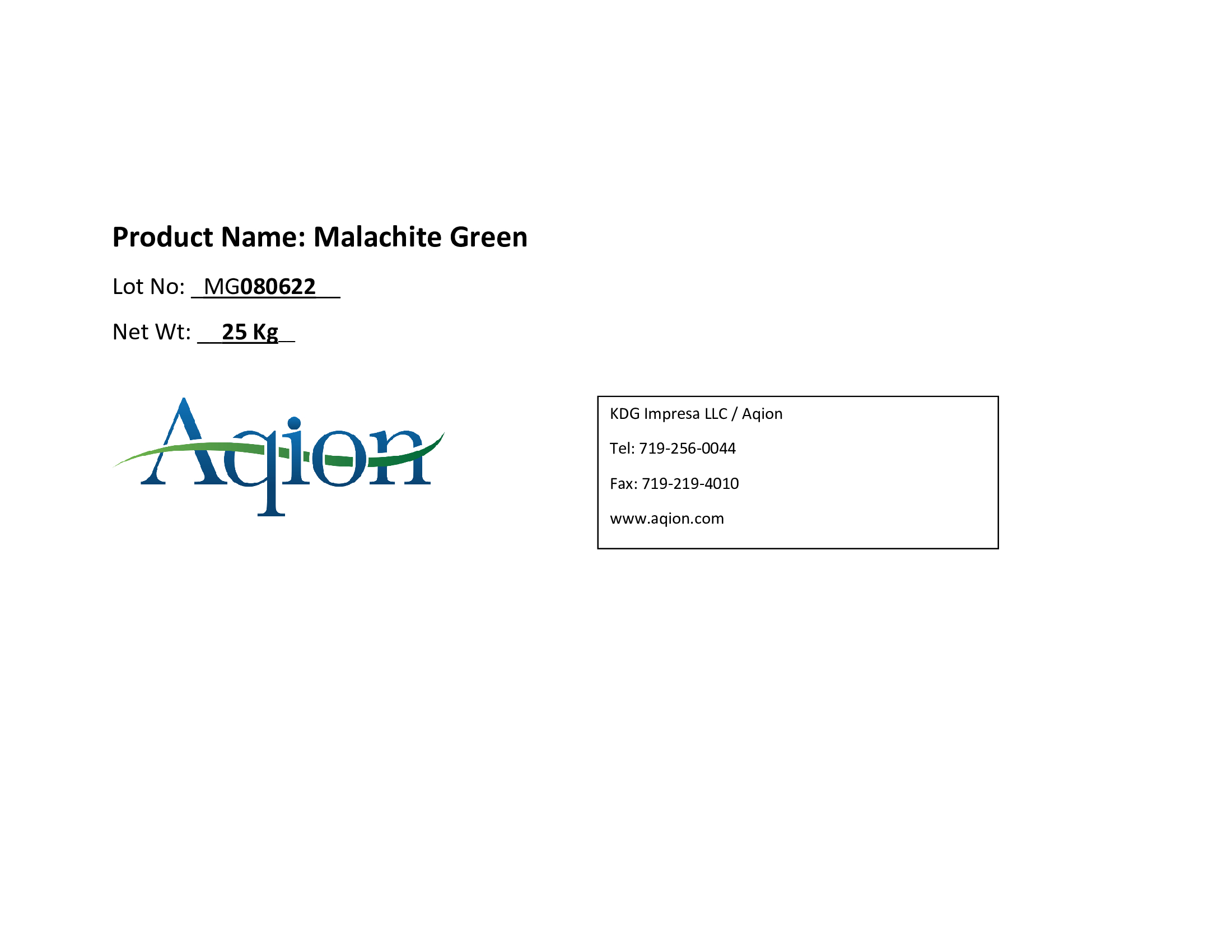 DRUG LABEL: Malachite Green
NDC: 43457-652 | Form: CRYSTAL
Manufacturer: KDG Impresa LLC, Aqion
Category: other | Type: BULK INGREDIENT - ANIMAL DRUG
Date: 20231207

ACTIVE INGREDIENTS: MALACHITE GREEN 1 kg/1 kg

Malachite Green